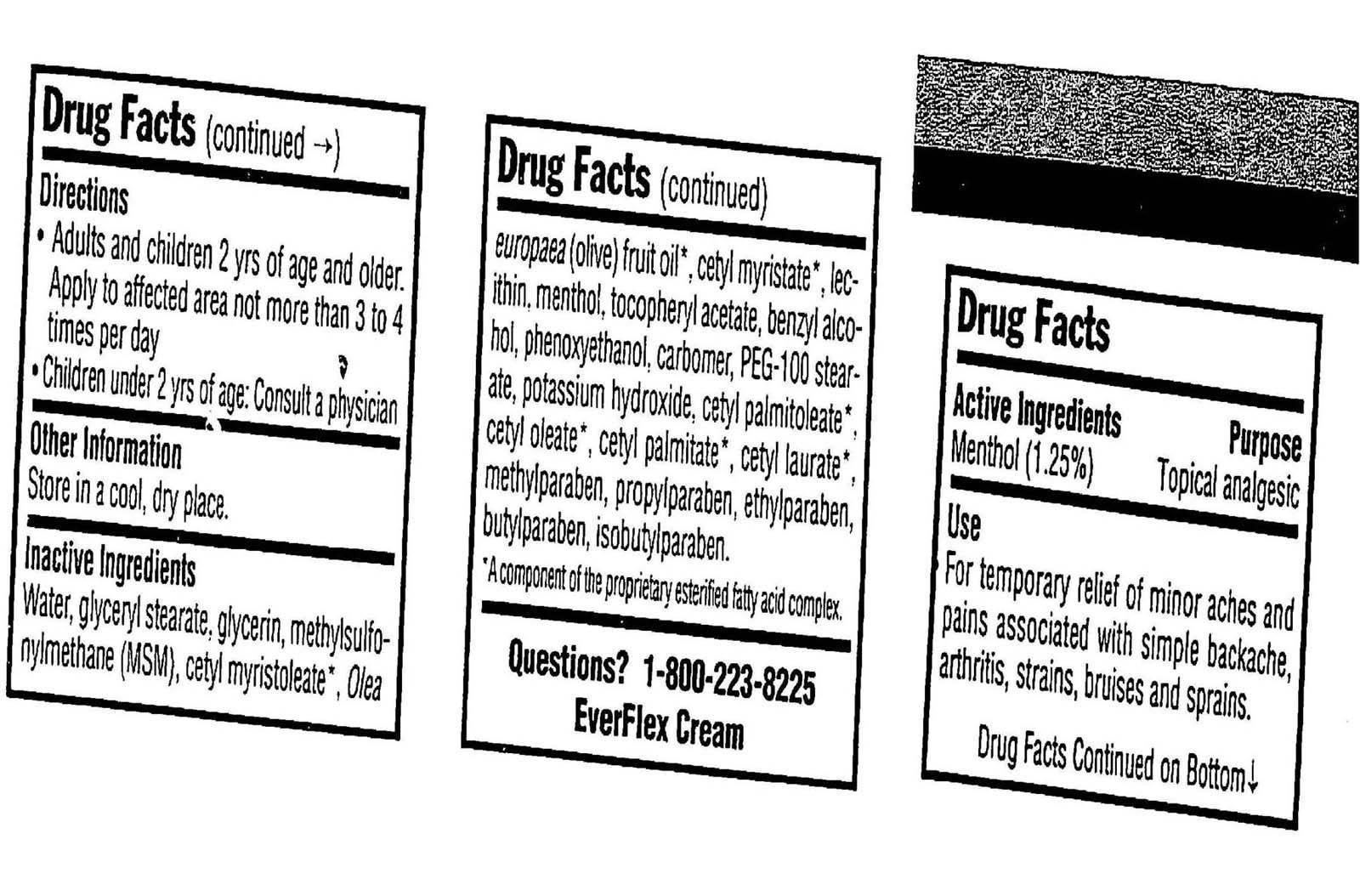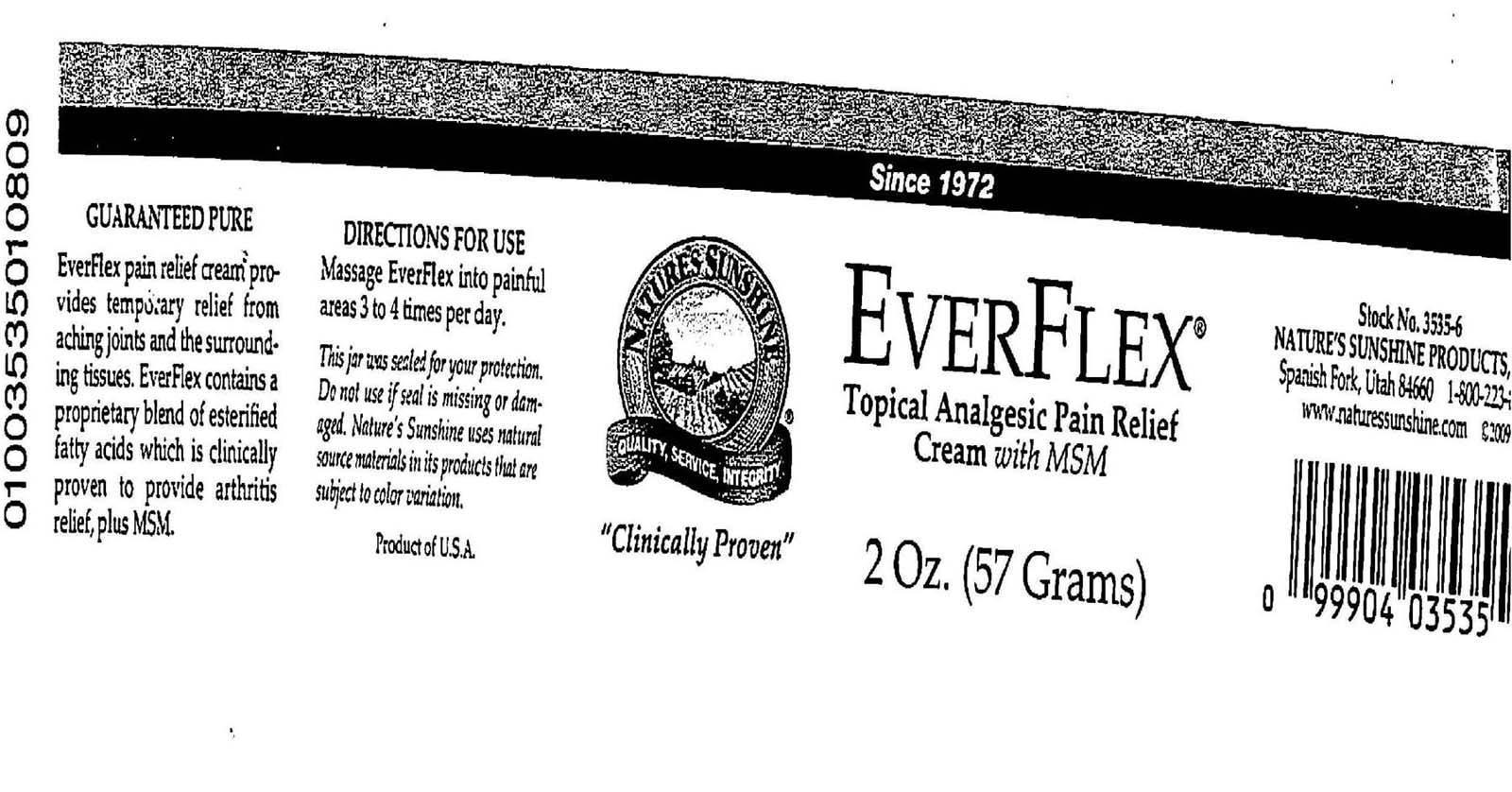 DRUG LABEL: Natures Sunshine Products
NDC: 61582-532 | Form: CREAM
Manufacturer: Natures Sunshine Products, Inc. 
Category: otc | Type: HUMAN OTC DRUG LABEL
Date: 20170522

ACTIVE INGREDIENTS: MENTHOL 1.25 g/100 g
INACTIVE INGREDIENTS: GLYCERYL MONOSTEARATE; GLYCERIN; CETYL MYRISTOLEATE; OLIVE OIL; CETYL MYRISTATE; BENZYL ALCOHOL; PHENOXYETHANOL; PEG-100 STEARATE; POTASSIUM HYDROXIDE; CETYL PALMITOLEATE; CETYL OLEATE; CETYL PALMITATE; METHYLPARABEN; PROPYLPARABEN; ETHYLPARABEN; BUTYLPARABEN; ISOBUTYLPARABEN

Everflex Topical Analgesic Pain Relief Cream

Active Ingredients Purpose
Menthol 1.25% Topical analgesic

PURPOSE

Everflex pain relief cream provides temporary relief from aching joints and the surrounding tissues. Ever flex contains a proprietary blend of esterified fatty acids which is clinically proven to provide arthritis relief, plus MSM.

-Keep out of reach of children

INDICATIONS AND USAGE

-If condition worsens, or if symptoms persist for more than 7 days or clear up and occur again within a few days, discontinue use of product and consult a physician
-Do not apply to wounds or damaged skin
-Do not bandage tightly
Other Information: Store in a cool, dry place.

WARNINGS

-For external use only
-Avoid contact with eyes

DOSAGE AND ADMINISTRATION

Directions for use: Massage Everflex into painful areas 3 to 4 times per day.

INACTIVE INGREDIENT

Inactive Ingredients: Water, Glyceryl Stearate, Glycerin, Methylsulfonylmethane (MSM), Cetyl Myristoleate, Olea Europaea (Olive) Fruit Oil, Cetyl Myristate, Lecithin, Menthol, Tocopheryl Acetate, Benzyl Alcohol, Phenoxyethanol, Carbomber, PEG-100 Stearate, Potassium Hydroxide, Cetyl Palmitoleate, Cetyl Oleate, Cetyl Palmitate, Cetyl Laurate, Methylparaben, Propylparaben, Ethylparaben, Butylparaben, Isobutylparaben.

PACKAGE LABEL

Everflex Topical Analgesic Pain Relief Cream with MSM
2 Oz. (57 Grams)